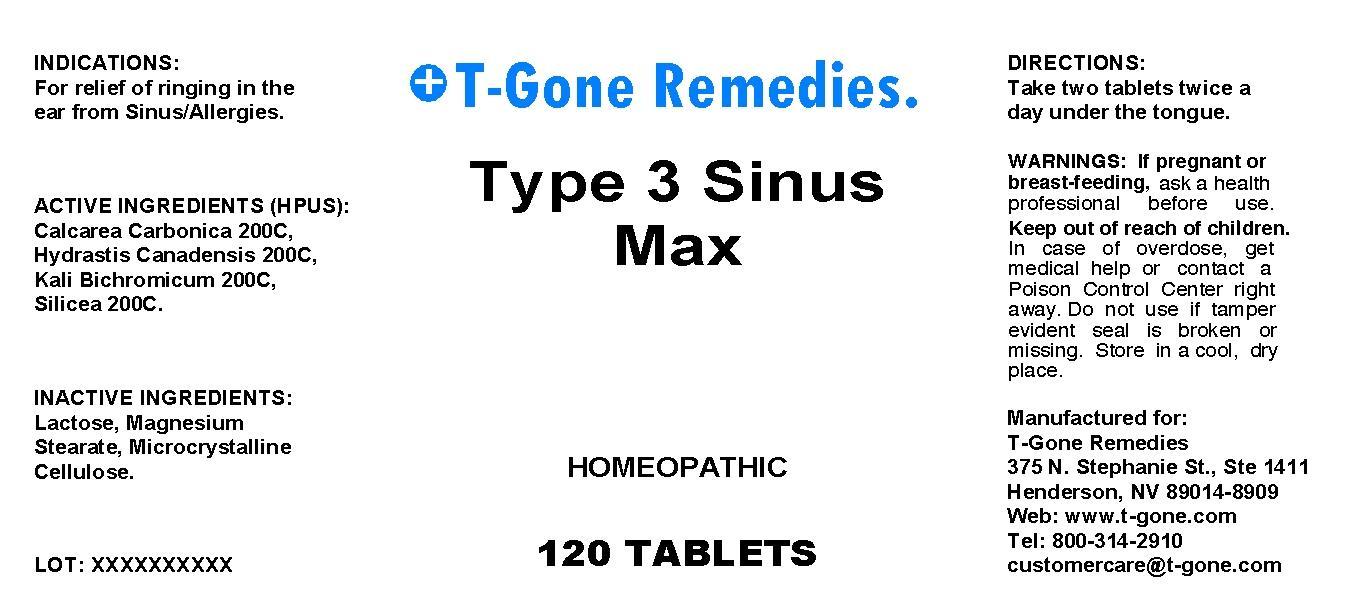 DRUG LABEL: Type 3 Sinus Max
NDC: 50169-0005 | Form: TABLET, ORALLY DISINTEGRATING
Manufacturer: TGone Remedies Ltd
Category: otc | Type: HUMAN OTC DRUG LABEL
Date: 20130905

ACTIVE INGREDIENTS: OYSTER SHELL CALCIUM CARBONATE, CRUDE 200 [hp_C]/1 1; GOLDENSEAL 200 [hp_C]/1 1; POTASSIUM DICHROMATE 200 [hp_C]/1 1; SILICON DIOXIDE 200 [hp_C]/1 1
INACTIVE INGREDIENTS: LACTOSE; MAGNESIUM STEARATE; CELLULOSE, MICROCRYSTALLINE

DRUG FACTS:

ACTIVE INGREDIENTS:

Calcare Carbonica 200C, Hydrastis Canadensis 200C, Kali Bichromicum 200C, Silicea 200C.

INDICATIONS:

For relief of ringing in the ear from Sinus/Allergies.

WARNINGS:

If pregnant or breast-feeding, ask a health professional before use.

Keep out of reach of children. In case of overdose, get medical help or contact a Poison Control Center right away.

Do not use if tamper evident seal is broken or missing.

Store in a cool, dry place.

Keep out of reach of children. In case of overdose, get medical help or contact a Poison Control Center right away.

DIRECTIONS:

Take two tablets twice a day under the tongue.

INDICATIONS:

For relief of ringing in the ear from Sinus/Allergies.

INACTIVE INGREDIENTS:

Lactose, Manesium Stearate, Microcrystalline Cellulose.

QUESTIONS:

Manufactured for:

T-Gone Remedies

375 N. Stephanie St., Ste 1411

Henderson, NV 89014-8909

Web: ww.t-gone.com

Tel: 800-314-2910

customercare@t-gone.com

PACKAGE DISPLAY LABEL:

T-Gone Remedies.

Type 3 Sinus Max

HOMEOPATHIC

120 TABLETS